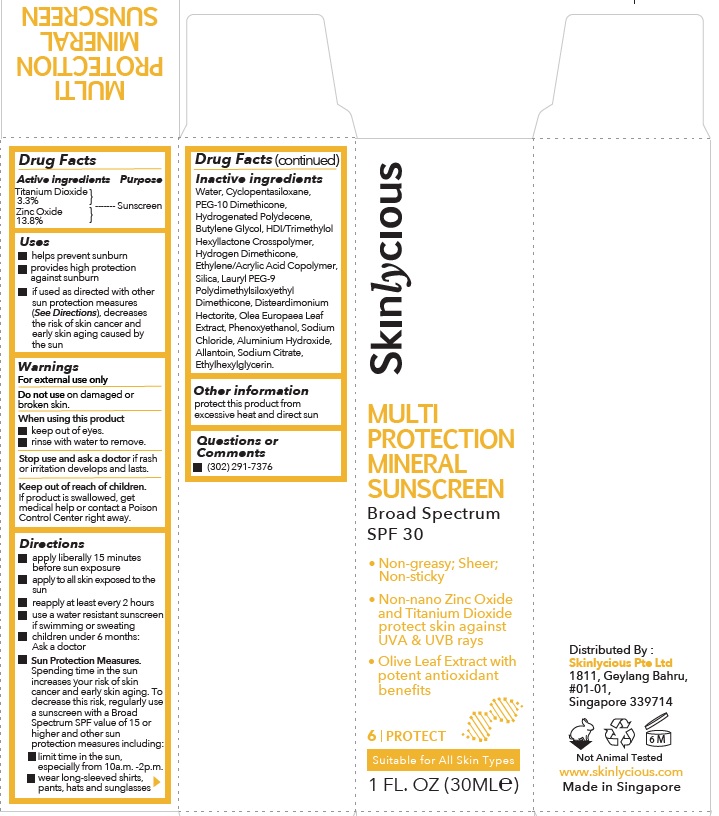 DRUG LABEL: Skinlycious Multi Protection Mineral Sunscreen Broad Spectrum SPF 30
NDC: 81574-002 | Form: CREAM
Manufacturer: Skinlycious Pte Ltd
Category: otc | Type: HUMAN OTC DRUG LABEL
Date: 20251013

ACTIVE INGREDIENTS: TITANIUM DIOXIDE 3.3 g/100 mL; ZINC OXIDE 13.8 g/100 mL
INACTIVE INGREDIENTS: CYCLOMETHICONE 5; PEG-10 DIMETHICONE (600 CST); HYDROGENATED POLYDECENE TYPE I; BUTYLENE GLYCOL; HEXAMETHYLENE DIISOCYANATE/TRIMETHYLOL HEXYLLACTONE CROSSPOLYMER; HYDROGEN DIMETHICONE (13 CST); ACRYLIC ACID/ETHYLENE COPOLYMER (600 MPA.S); SILICON DIOXIDE; LAURYL PEG-9 POLYDIMETHYLSILOXYETHYL DIMETHICONE; DISTEARDIMONIUM HECTORITE; OLEA EUROPAEA LEAF; PHENOXYETHANOL; SODIUM CHLORIDE; ALUMINUM HYDROXIDE; ALLANTOIN; SODIUM CITRATE; WATER; ETHYLHEXYLGLYCERIN

Active ingredients

Titanium Dioxide 3.3%

Zinc Oxide 13.8%

Purpose

Sunscreen

Uses

• helps prevent sunburn
• provides high protection against sunburn
• if used as directed with other sun protection measures (See Directions), decreases the risk of skin cancer and early skin aging caused by the sun

Warnings

For External Use Only
Do not use ondamaged or broken skin.
When using this product
• Keep out of eyes.
• Rinse with water to remove.

Stop use and ask a doctorif rash or irritation develops and lasts.

Keep out of reach of children

If product is swallowed, get medical help or contact a Poison Control Center right away.

Directions

• Apply liberally 15 minutes before sun exposure.
• Apply to all skin exposed to the sun.
• Reapply at least every 2 hours.
• Use a water resistant sunscreen if swimming or sweating.
• Children under 6 months: ask a doctor.
• Sun Protection Measures Spending time in the sun increases your risk of skin cancer and early skin aging. To decrease this risk, regularly use a sunscreen with a Broad Spectrum SPF value of 15 or higher and other sun protection measures including :
- limit time in the sun, especially from 10a.m.-2p.m.
- wear long-sleeved shirts, pants, hats and sunglasses.

Inactive Ingredients

Water, Cyclopentasiloxane, PEG-10 Dimethicone, Hydrogenated Polydecene, Butylene Glycol, HDI/Trimethylol Hexyllactone Crosspolymer, Hydrogen Dimethicone, Ethylene/Acrylic Acid Copolymer, Silica, Lauryl PEG-9 Polydimethylsiloxyethyl Dimethicone, Disteardimonium Hectorite, Olea Europaea Leaf Extract, Phenoxyethanol, Sodium Chloride, Aluminium Hydroxide, Allantoin, Sodium Citrate, Ethylhexylglycerin.

Other information

• protect this product from excessive heat and direct sun

Questions or comments

(302) 291-7376